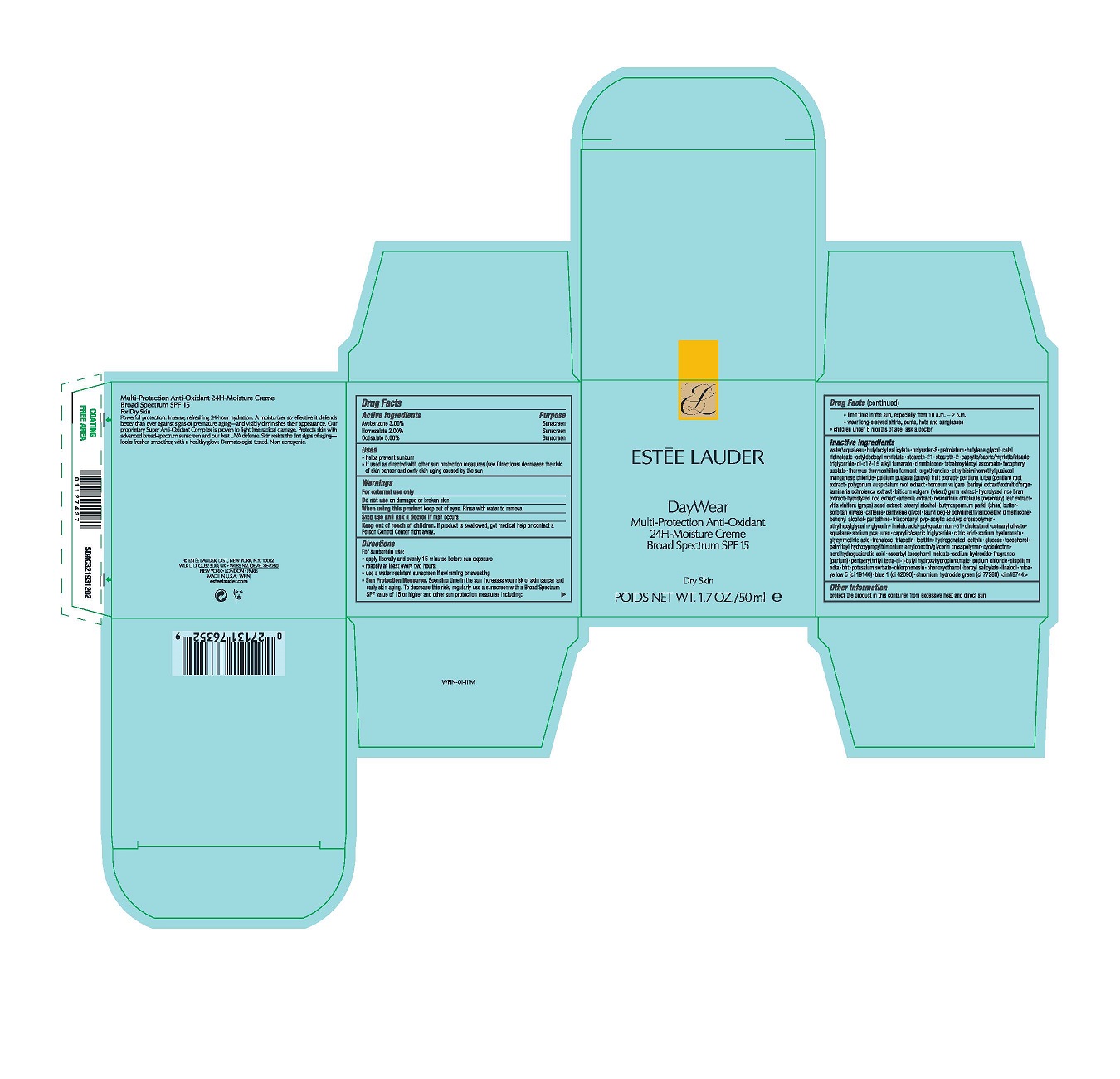 DRUG LABEL: DAYWEAR ADVANCED MULTI-PROTECTION ANTI-OXIDANT 24H-MOISTURE CREME BROAD SPECTRUM SPF15
NDC: 11559-064 | Form: CREAM
Manufacturer: ESTEE LAUDER INC
Category: otc | Type: HUMAN OTC DRUG LABEL
Date: 20231113

ACTIVE INGREDIENTS: AVOBENZONE 30 mg/1 mL; HOMOSALATE 20 mg/1 mL; OCTISALATE 50 mg/1 mL
INACTIVE INGREDIENTS: DI-C12-15 ALKYL FUMARATE; VITIS VINIFERA SEED; ETHYLHEXYLGLYCERIN; GLYCERIN; CITRIC ACID MONOHYDRATE; SODIUM CHLORIDE; CHLORPHENESIN; PHENOXYETHANOL; WATER; POLYESTER-8 (1400 MW, CYANODIPHENYLPROPENOYL CAPPED); SORBITAN OLIVATE; CETEARYL OLIVATE; ANHYDROUS DEXTROSE; BUTYLOCTYL SALICYLATE; CAPRYLIC/CAPRIC/MYRISTIC/STEARIC TRIGLYCERIDE; ETHYLBISIMINOMETHYLGUAIACOL MANGANESE CHLORIDE; LAMINARIA OCHROLEUCA; TRIACONTANYL PVP (WP-660); LINOLEIC ACID; SODIUM PYRROLIDONE CARBOXYLATE; HYALURONATE SODIUM; ENOXOLONE; HYDROGENATED SOYBEAN LECITHIN; LINALOOL, (+/-)-; MICA; CHROMIUM HYDROXIDE GREEN; STEARETH-21; DIMETHICONE; GENTIANA LUTEA ROOT; WHEAT GERM; STEARETH-2; DOCOSANOL; POLYQUATERNIUM-51 (2-METHACRYLOYLOXYETHYL PHOSPHORYLCHOLINE/N-BUTYL METHACRYLATE; 3:7); MEDIUM-CHAIN TRIGLYCERIDES; CYCLODEXTRINS; ASCORBYL TOCOPHERYL MALEATE; POLYGONUM CUSPIDATUM ROOT; ROSEMARY; STEARYL ALCOHOL; LAURYL PEG-9 POLYDIMETHYLSILOXYETHYL DIMETHICONE; TREHALOSE; MASOPROCOL; EDETATE DISODIUM ANHYDROUS; BENZYL SALICYLATE; CETYL RICINOLEATE; TETRAHEXYLDECYL ASCORBATE; GUAVA; CAFFEINE; PENTYLENE GLYCOL; PANTETHINE; SQUALANE; TRIACETIN; OCTYLDODECYL MYRISTATE; ALPHA-TOCOPHEROL ACETATE; THERMUS THERMOPHILUS LYSATE; ERGOTHIONEINE; LECITHIN, SOYBEAN; TOCOPHEROL; PALMITOYL HYDROXYPROPYLTRIMONIUM AMYLOPECTIN/GLYCERIN CROSSPOLYMER; SODIUM HYDROXIDE; BUTYLATED HYDROXYTOLUENE; FD&C YELLOW NO. 5; PETROLATUM; HORDEUM VULGARE WHOLE; SHEA BUTTER; CHOLESTEROL; POTASSIUM SORBATE; UREA; PENTAERYTHRITOL TETRAKIS(3-(3,5-DI-TERT-BUTYL-4-HYDROXYPHENYL)PROPIONATE); FD&C BLUE NO. 1; BUTYLENE GLYCOL

DAYWEAR ADVANCED MULTI-PROTECTION ANTI-OXIDANT 24H-MOISTURE CREME BROAD SPECTRUM SPF15

Active Ingredients

AVOBENZONE 3.0%
HOMOSALATE 2.0%
OCTISALATE 5.0%

Purpose

Sunscreen

Uses

-helps precent sunburn

-if used as directed with other sun protection measures (see Directions) decreases the risk of skin cancer and early skin aging cause by the seun

Warnings

For external use only

Do not use

on damaged or broken skin

When using this product

keep out of eye. Rinse with water to remove

Stop use and ask a doctor

if rash occurs

Keep out of reach of children.

If product is swallowed, get medical help or contact a Poison Control Center right away.

Directions

For sunscreen use:
apply liberally 15 minutes before sun exposure
reapply at least every two hours
use a water resistant sunscreen if swimming or sweating
Sun Protection Measures. Spending time in the sun increases your risk of skin cancer and early skin aging. To decrease this risk, regularly use a sunscreen with a Broad Spectrum SPF value of 15 or higher and other sun protection measures including:
limit time in the sun, especially from 10 a.m.–2 p.m.
wear long-sleeved shirts, pants, hats and sunglasses
children under 6 months of age: ask a doctor

Inactive Ingredients

WATER\AQUA\EAU,BUTYLOCTYL SALICYLATE,POLYESTER-8,PETROLATUM,BUTYLENE GLYCOL,CETYL RICINOLEATE,OCTYLDODECYL MYRISTATE,STEARETH-21,STEARETH-2,CAPRYLIC/CAPRIC/MYRISTIC/STEARIC TRIGLYCERIDE,DI-C12-15 ALKYL FUMARATE,DIMETHICONE,TETRAHEXYLDECYL ASCORBATE,TOCOPHERYL ACETATE,THERMUS THERMOPHILLUS FERMENT,ERGOTHIONEINE,ETHYLBISIMINOMETHYLGUAIACOL MANGANESE CHLORIDE,PSIDIUM GUAJAVA (GUAVA) FRUIT EXTRACT,GENTIANA LUTEA (GENTIAN) ROOT EXTRACT,POLYGONUM CUSPIDATUM ROOT EXTRACT,HORDEUM VULGARE (BARLEY) EXTRACT\EXTRAIT D'ORGE,LAMINARIA OCHROLEUCA EXTRACT,TRITICUM VULGARE (WHEAT) GERM EXTRACT,HYDROLYZED RICE BRAN EXTRACT,HYDROLYZED RICE EXTRACT,ARTEMIA EXTRACT,ROSMARINUS OFFICINALIS (ROSEMARY) LEAF EXTRACT,VITIS VINIFERA (GRAPE) SEED EXTRACT,STEARYL ALCOHOL,BUTYROSPERMUM PARKII (SHEA) BUTTER,SORBITAN OLIVATE,CAFFEINE,PENTYLENE GLYCOL,LAURYL PEG-9 POLYDIMETHYLSILOXYETHYL DIMETHICONE,BEHENYL ALCOHOL,PANTETHINE,TRIACONTANYL PVP,ACRYLIC ACID/VP CROSSPOLYMER,ETHYLHEXYLGLYCERIN,GLYCERIN,LINOLEIC ACID,POLYQUATERNIUM-51,CHOLESTEROL,CETEARYL OLIVATE,SQUALANE,SODIUM PCA,UREA,CAPRYLIC/CAPRIC TRIGLYCERIDE,CITRIC ACID,SODIUM HYALURONATE,GLYCYRRHETINIC ACID,TREHALOSE,TRIACETIN,LECITHIN,HYDROGENATED LECITHIN,GLUCOSE,TOCOPHEROL,PALMITOYL HYDROXYPROPYLTRIMONIUM AMYLOPECTIN/GLYCERIN CROSSPOLYMER,CYCLODEXTRIN,NORDIHYDROGUAIARETIC ACID,ASCORBYL TOCOPHERYL MALEATE,SODIUM HYDROXIDE,FRAGRANCE (PARFUM),PENTAERYTHRITYL TETRA-DI-T-BUTYL HYDROXYHYDROCINNAMATE,SODIUM CHLORIDE,DISODIUM EDTA,BHT,POTASSIUM SORBATE,CHLORPHENESIN,PHENOXYETHANOL,BENZYL SALICYLATE,LINALOOL,MICA,YELLOW 5 (CI 19140),BLUE 1 (CI 42090),CHROMIUM HYDROXIDE GREEN (CI 77289) <ILN48744>

Other information

protect the product in this container from excessive heat and direct sun

PACKAGE LABEL

Estee Lauder

DayWear

Multi-Protection Anti-Oxidant
24H-Moisture Creme

Broad Spectrum SPF15

Dry Skin

POIDS NET WT. 1.7OZ/5.ml e